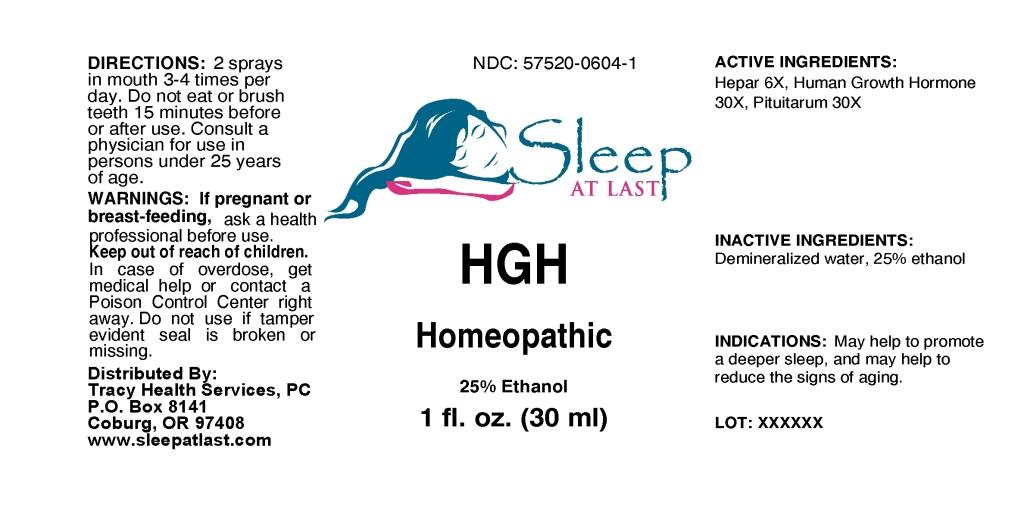 DRUG LABEL: HGH
NDC: 57520-0604 | Form: LIQUID
Manufacturer: Apotheca Company
Category: homeopathic | Type: HUMAN OTC DRUG LABEL
Date: 20110217

ACTIVE INGREDIENTS: PORK LIVER 6 [hp_X]/1 mL; SOMATROPIN 30 [hp_X]/1 mL; SUS SCROFA PITUITARY GLAND 30 [hp_X]/1 mL
INACTIVE INGREDIENTS: WATER; ALCOHOL

HGH

ACTIVE INGREDIENT

ACTIVE INGREDIENTS: Hepar 6X, Human growth hormone 30X, Pituitarum 30X.

PURPOSE

INDICATIONS: May help to promote a deeper sleep, and may help to reduce the signs of aging.

WARNINGS

WARNINGS: If pregnant or breast-feeding, ask a health professional before use.

Keep out of reach of children. In case of overdose, get medical help or contact a Poison Control Center right away.

Do not use if tamper evident seal is broken or missing.

DOSAGE AND ADMINISTRATION

DIRECTIONS: 2 sprays in mouth 3-4 times per day. Do not eat or brush teeth 15 minutes before or after use. Consult a physician for use in persons under 25 years of age.

INACTIVE INGREDIENTS: Demineralized water, 25% Ethanol.

KEEP OUT OF REACH OF CHILDREN. In case of overdose, get medical help or contact a Poison Control Center right away.

INDICATIONS AND USAGE

INDICATIONS: May help to promote a deeper sleep, and may help to reduce the signs of aging.

QUESTIONS

Distributed By:

Tracy Health Services, PC

P.O. Box 8141

Coburg, OR 97408

www.sleepatlast.com

PACKAGE LABEL

NDC: 57520-0604-1

Sleep AT LAST

HGH

Homeopathic

1 fl. oz. (30 ml)